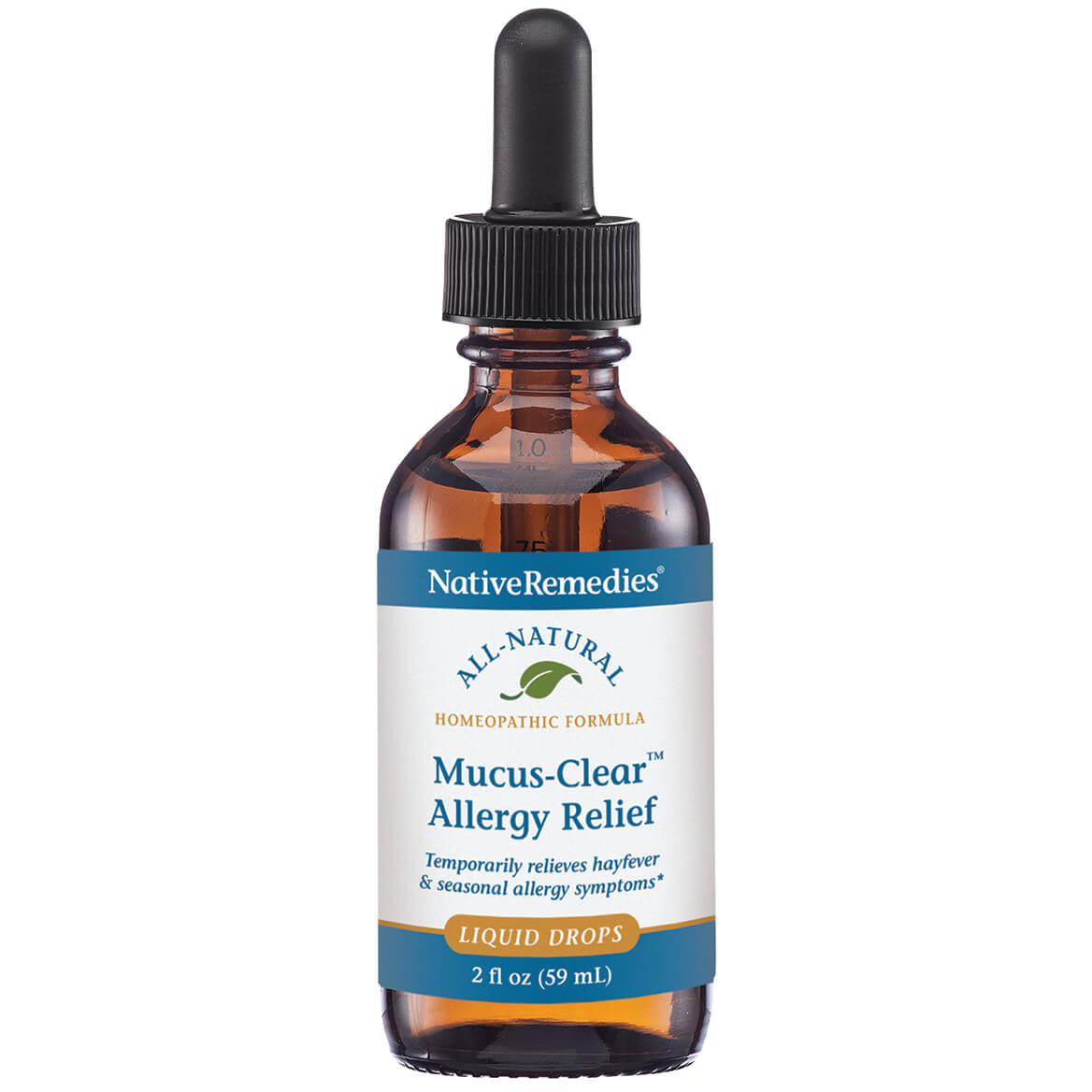 DRUG LABEL: Mucus Clear Allergy Relief
NDC: 68703-386 | Form: LIQUID
Manufacturer: Silver Star Brands
Category: homeopathic | Type: HUMAN OTC DRUG LABEL
Date: 20250101

ACTIVE INGREDIENTS: EUPHRASIA STRICTA 30 [hp_X]/59 mL; SODIUM CHLORIDE 30 [hp_X]/59 mL; PULSATILLA PATENS WHOLE 30 [hp_X]/59 mL; ONION 30 [hp_X]/59 mL; POTASSIUM CHLORIDE 30 [hp_X]/59 mL; STRYCHNOS IGNATII SEED 30 [hp_X]/59 mL; STRYCHNOS NUX-VOMICA SEED 30 [hp_X]/59 mL; CALCIUM PHOSPHATE 30 [hp_X]/59 mL; SILICON DIOXIDE 30 [hp_X]/59 mL
INACTIVE INGREDIENTS: WATER; POTASSIUM SORBATE; ANHYDROUS CITRIC ACID

NativeRemedies® Mucus-Clear™ Allergy Relief

HPUS Active Ingredients: Equal volumes of each ingredient in a 10X, 15X, 30X potency: Alliu cepa, Calc phos, Euphrasia, Ignatia, Kali mur, Nat mur, Nux bom, Pulsatilla, Silica.

The letters HPUS indicate that the components in this product are officially monographed in the Homeopathic Pharmacopoeia of the United States.

Uses*

Uses*: Homeopathic relief from the sneezing, runny nose, excess mucus, and red, itchy, watery eyes caused by hayfever and seasonal allergies.

*Claims based on traditional homeopathic practice, not accepted medical evidence. Not FDA evaluated.

Warnings

Warnings: If symptoms persist or worsen, consult a healthcare professional. If pregnant or breastfeeding, ask a health professional before use. Keep this and all medication out of reach of children. In case of overdose, get medical help or contact a Poison Control Center right away.

Directions

Directions: Mix drops in 1/4 cup of water and sip slowly. Adults and children 12+: 0.50 mL 3-5 times daily. Children under 12: 0.25 mL 3-5 times daily. For acute symptoms, repeat every 15-20 minutes as needed up to 6 doses.

OTHER SAFETY INFORMATION

Contains no artificial flavors or colorants. No gluten added.

Tamper resistant for your protection. Use only if safety seal is intact.

Inactive Ingredients

Inactive Ingredients: Citric acid, Potassium sorbate, Purified water.

KEEP OUT OF REACH OF CHILDREN

Keep this and all medications out of reach of children.

PREGNANCY OR BREAST FEEDING

If pregnant or breastfeeding, ask a health professional before use.

PURPOSE

Temporarily relieves hayfever & seasonal allergy symptoms.